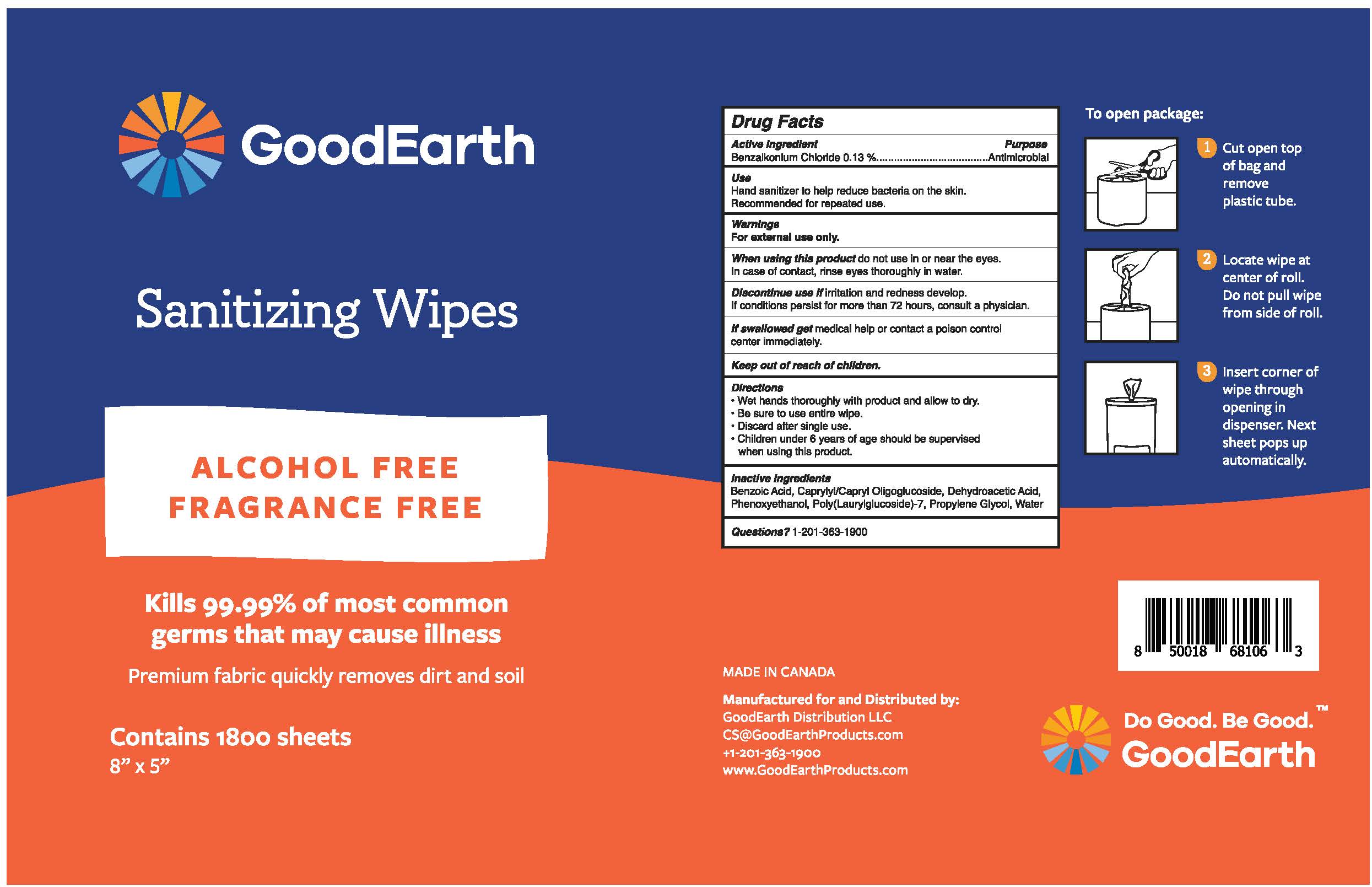 DRUG LABEL: Sanitizing Wipes
NDC: 71745-002 | Form: CLOTH
Manufacturer: GoodEarth Distribution Llc
Category: otc | Type: HUMAN OTC DRUG LABEL
Date: 20250619

ACTIVE INGREDIENTS: BENZALKONIUM CHLORIDE 1.3 mg/1 1
INACTIVE INGREDIENTS: PROPYLENE GLYCOL; CAPRYLYL/CAPRYL OLIGOGLUCOSIDE; WATER; POLY(LAURYLGLUCOSIDE)-7; PHENOXYETHANOL; BENZOIC ACID; DEHYDROACETIC ACID

Sanitizing Wipes Alcohol Free Fragrance Free

Drug Facts

Active ingredient

Benzalkonium Chloride 0.13 %

Purpose

Antimicrobal

Use

Hand sanitizer to help reduce bacteria on the skin.

Recommended for repeated use.

Warnings

For external use only.

When using this product do not use in or near the eyes. In case of contact, rinse eyes thoroughly in water.

STOP USE

Discontinue use if irritation and redness develop. If conditions persist for more than 72 hours, consult a physician.

If swallowed get medical help or contact a poison control center immediately.

Keep out of reach of children.

Directions

- Wet hands thoroughly with product and allow to dry.
- Be sure to use entire wipe.
- Discard after single use.
- Children under 6 years of age should be supervised when using this product.

Inactive ingredients

Benzoic Acid, Caprylyl/Capryl Oligoglucoside, Dehydroacetic Acid, Phenoxyethanol, Poly(Laurylglucoside)-7, Propylene Glycol, Water

Questions

Questions? 1-201-363-1900

PACKAGE LABEL

GoodEarth

Sanitizing Wipes

ALCOHOL FREE

FRAGRANCE FREE

Kills 99.99% of most common

germs that may cause illness

Premium fabric quickly removes dirt and soil

Contains 1800 sheets

8" x 5"

To open package:

1 Cut open top

of bag and

remove

plastic tube.

2 Locate wipe at

center of roll.

Do not pull wipe

from side of roll.

3 Insert corner of

wipe through

opening in

dispenser. Next

sheet pops up

automatically.

MADE IN CANADA
Manufactured for and Distributed by:
GoodEarth Distribution LLC
CS@GoodEarthProducts.com
+1-201-363-1900
www.GoodEarthProducts.com

Do Good. Be Good. TM

GoodEarth